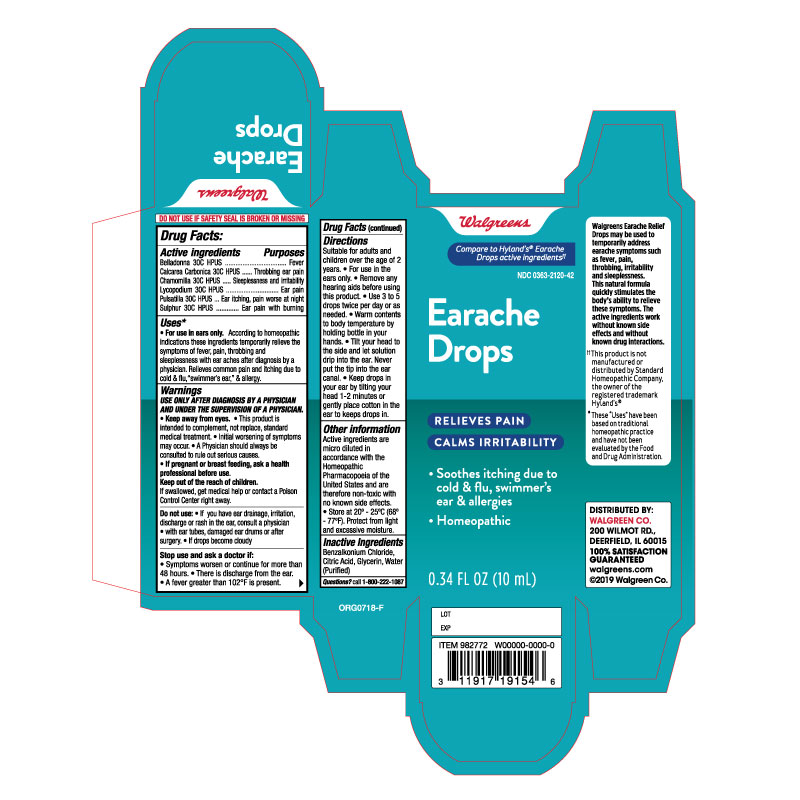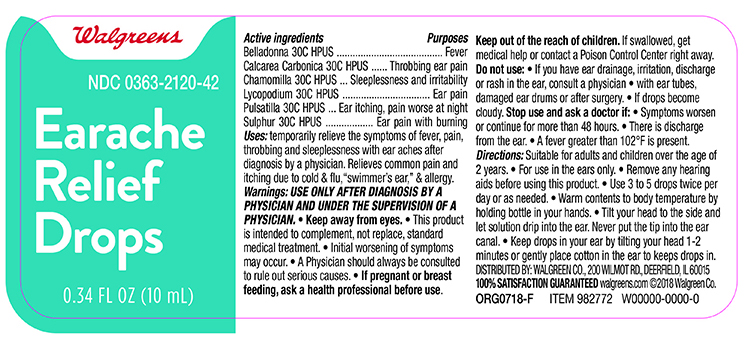 DRUG LABEL: Walgreens Earache Drops
NDC: 0363-2120 | Form: SOLUTION/ DROPS
Manufacturer: Walgreens Co
Category: homeopathic | Type: HUMAN OTC DRUG LABEL
Date: 20191213

ACTIVE INGREDIENTS: ATROPA BELLADONNA 30 [hp_C]/1 mL; OYSTER SHELL CALCIUM CARBONATE, CRUDE 30 [hp_C]/1 mL; MATRICARIA CHAMOMILLA 30 [hp_C]/1 mL; LYCOPODIUM CLAVATUM SPORE 30 [hp_C]/1 mL; ANEMONE PULSATILLA 30 [hp_C]/1 mL; SULFUR 30 [hp_C]/1 mL
INACTIVE INGREDIENTS: GLYCERIN; BENZALKONIUM CHLORIDE; CITRIC ACID MONOHYDRATE; WATER

Drug Facts

Active ingredient

Belladonna 30C HPUS, Calcarea Carbonica 30C HPUS, Chamomilla 30C HPUS, Lycopodium Clavatum 30C HPUS, Pulsatilla 30C HPUS, Sulphur 30C HPUS

Purpose

Fever, Throbbing ear pain, Sleeplessness and irritability, Ear pain, Ear itching pain worse at night , Ear pain with burning

Uses

For use I ear only, according to homeopathic indications these ingredients temporaily relieve the symptoms of fever, pain, throbbing and sleeplessness, with ear aches after diagnosis by a physician. Relieves common pain and itching due ot cold and flu "swimmers ear "& allergies.

Warnings

Use only after diagonsis by a physcian and under the supervisor or a physcian

Keep away from eyes

- this product is intended or compliment , not replace standard medical treatment
- initial worsening of symptoms may occur
- A Physician should always be consulted to rule out serious causes

If pregnant or breast feeding, ask a health care professional before use.

Stop Use and ask a Doctor if

- Symptoms worsenor continue for more than 48 hours
- There is dischare for the ear
- A fever greater than 102°F is present

Do not use

- If if you have irritation, discharge or rash in the ear, consult a physician
- with ear tube, damaged ear drums or after surgery
- If product becomes cloudy

When using this product

- do not use for more than four days
- avoid contact with the eyes. If accidental contact with the eyes occurs, flush eyes with water and consult a doctor
- if excessive earwax remains after the use of this product, consult a doctor

Keep out of the reach of children

If swallowed, get medical help or contact a Poison Control Center right away.

Directions FOR USE IN THE EAR ONLY

- Adults and children over the age of 2 years :
- For use in the ear only
- Remove any hearing aids before using this product
- Use 3 to 5 drops twice per day or as needed
- Warm the content to body temperature by holding in your hands
- Tilt head sideways and let solution drip into ear.
- Tip of applicator should not enter ear canal.
- Keep drops in ear for 1 to 2 minutes by keeping head tilted or placing cotton in the ear.

Other information

- Protect from light and excessive moisture
- Active ingredient are micro dilutions in accordance with the Homeopathic Pharmacopeia of the United States and are therefore non toxic with no known side effects

Inactive ingredients

Benzalkonium Chloride, Citric Acid, Glycerin, Water

Principal Display Panel -Bottle Label 0.34 FLOZ

Walgreen NDC 0363-2120-42

Earache Drops

Homoepathic

- Releives Pain
- Calms Irritability

0.34 FLOZ (10ml)

Principal Display Panel Box label 0.34 FLOZ

Walgreens NDC 0363-2120-42

Eareache Drops

Homoepathic

- Relieves Pain
- Calms Irritability

0.34 FLOZ (10ml)